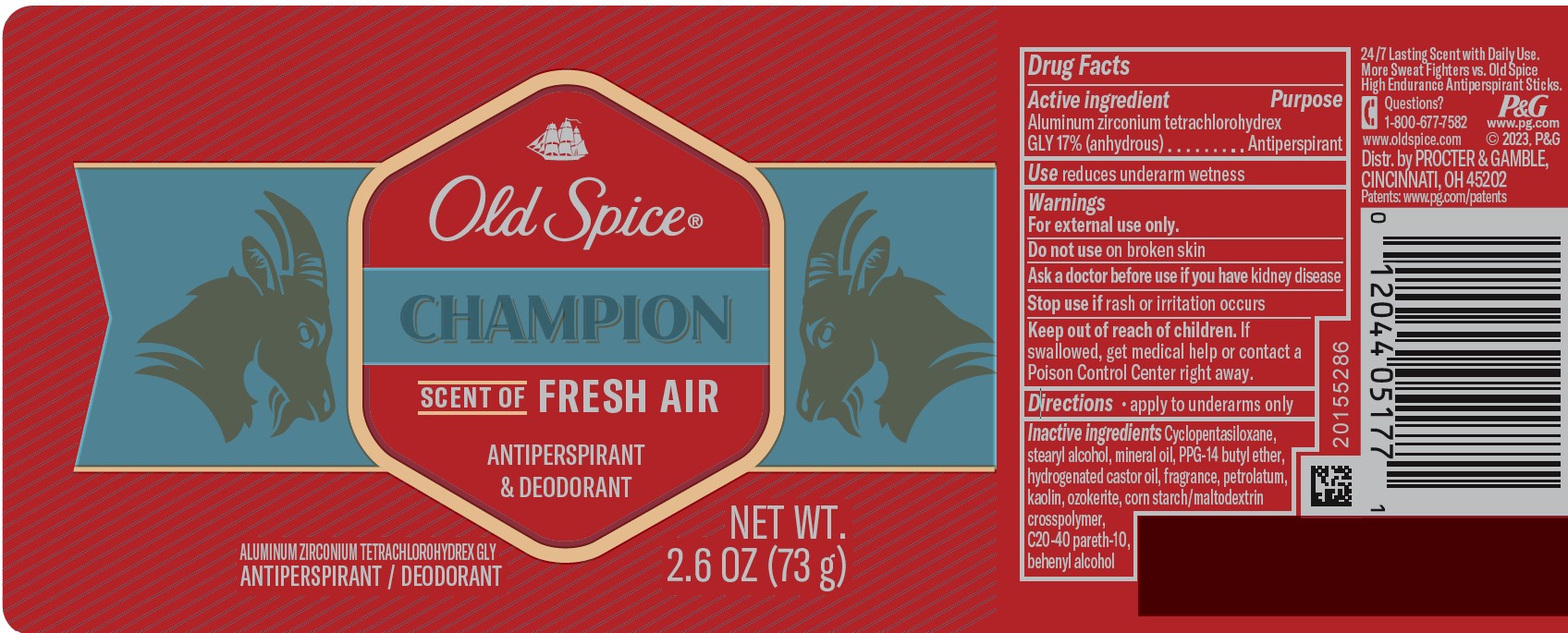 DRUG LABEL: Old Spice Champion Antiperspirant and Deodorant
NDC: 84126-067 | Form: STICK
Manufacturer: The Procter & Gamble Manufacturing Company
Category: otc | Type: HUMAN OTC DRUG LABEL
Date: 20251231

ACTIVE INGREDIENTS: ALUMINUM ZIRCONIUM TETRACHLOROHYDREX GLY 17 g/100 g
INACTIVE INGREDIENTS: CERESIN; CYCLOPENTASILOXANE; STEARYL ALCOHOL; MINERAL OIL; KAOLIN; HYDROGENATED CASTOR OIL; PPG-14 BUTYL ETHER; C20-40 PARETH-10; BEHENYL ALCOHOL; PETROLATUM

Old Spice® Champion

Drug Facts

Active ingredient

Aluminum zirconium tetrachlorohydrex Gly 17% (anhydrous)

Purpose

Antiperspirant

Use

reduces underarm wetness

Warnings

For external use only.

Do not use on broken skin

Ask a doctor before use if you have kidney disease

Stop use if rash or irritation occurs

Keep out of reach of children.
If swallowed, get medical help or contact a Poison Control Center right away.

Directions

- apply to underarms only

Inactive ingredients

Cyclopentasiloxane, stearyl alcohol, mineral oil, PPG-14 butyl ether, hydrogenated castor oil, fragrance, petrolatum, kaolin, ozokerite, corn starch/maltodextrin crosspolymer, C20-40 pareth-10, behenyl alcohol

Questions?

1-800-677-7582

Dist. by PROCTER & GAMBLE,
CINCINNATI, OH 45202.

PRINCIPAL DISPLAY PANEL - 73 g Cylinder Label

Old Spice ®

Champion

Scent of Fresh Air

ANTIPERSPIRANT & DEODORANT
ALUMINUM ZIRCONIUM

TETRACHLOROHYDREX GLY

ANTIPERSPIRANT / DEODORANT

NET WT. 2.6 OZ (73 g)